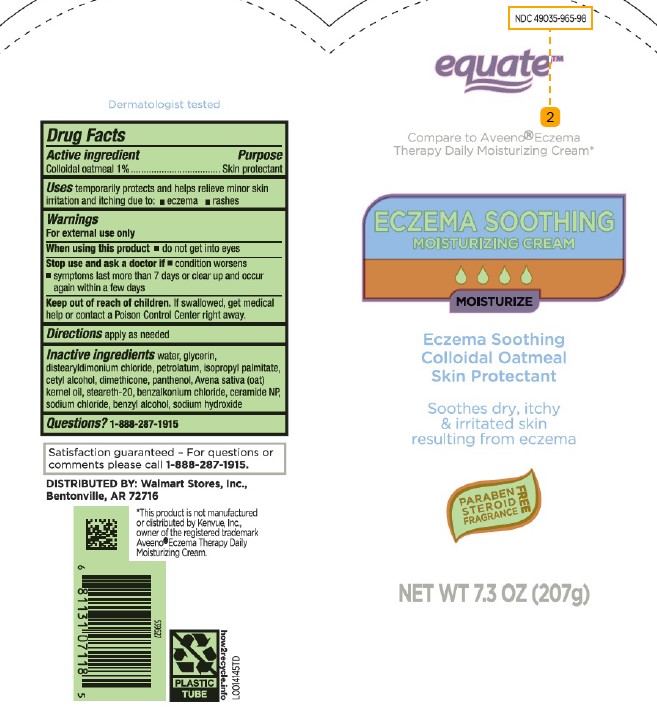 DRUG LABEL: Soothing Moisturizing
NDC: 49035-965 | Form: CREAM
Manufacturer: Walmart Inc.
Category: otc | Type: HUMAN OTC DRUG LABEL
Date: 20260227

ACTIVE INGREDIENTS: OATMEAL 10.4 mg/1 g
INACTIVE INGREDIENTS: WATER; GLYCERIN; DISTEARYLDIMONIUM CHLORIDE; PETROLATUM; ISOPROPYL PALMITATE; CETYL ALCOHOL; DIMETHICONE; PANTHENOL; OAT KERNEL OIL; STEARETH-20; BENZALKONIUM CHLORIDE; CERAMIDE 3; SODIUM CHLORIDE; BENZYL ALCOHOL; SODIUM HYDROXIDE

Equate 965.001/965AC
Eczema Soothing Moisturizing Cream

Claims

Dermatologist tested

Active ingredient

Colloidal oatmeal 1 %

Purpose

Skin protectant

Uses

temporarily protectes and helps relieve minor skin irritation and itching due to:

- eczema
- rashes

Warnings

For external use only

When using this product

- do not get into eyes

Stop use and ask a doctor if

- condition worsens
- symptoms last more than 7 days or clear up and occur again withing a few days

Keep out of reach of children

If swallowed, get medical help or contact a Poison Control Center right away.

Directions

apply as needed

inactive ingredients

water, glycerin, distearyldimonium chloride, petrolatum, isopropyl palmitate, cetyl alcohol, dimethicone, panthenol, Avena sativa (oat) kernel oil, steareth-20, benzalkonium chloride, ceramide NP, sodium chloride, benzyl alcohol, sodium hydroxide

Questions?

1-888-287-1915

ADVERSE REACTION

Satisfaction guaranteed - For questions or comments please call 1-888-287-1915

Distributed by:

Wal-Mart Stores, Inc.,

Bentonville, AR 72716

*This product is not manufactured or distributed by Kenvue, Inc., owner of the registered trademark Aveeno® Eczema Therapy Daily Moisturizing Cream.

principal display panel

NDC 49035-965-98

equate™

Compare to Aveeno® Eczema Therapy Daily Moisturizing Cream*

ECZEMA SOOTHING

MOISTURIZING CREAM

MOISTURIZE

Eczema Soothing

Colloidal Oatmeal

Skin Protectant

Soothes, dry, itchy & irritated skin resulting from eczema

FREE

PARABEN

STEROID

FRAGRANCE

NET WT 7.3 OZ (207 g)